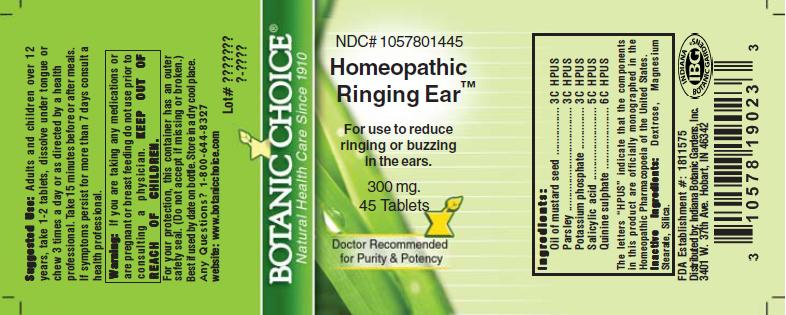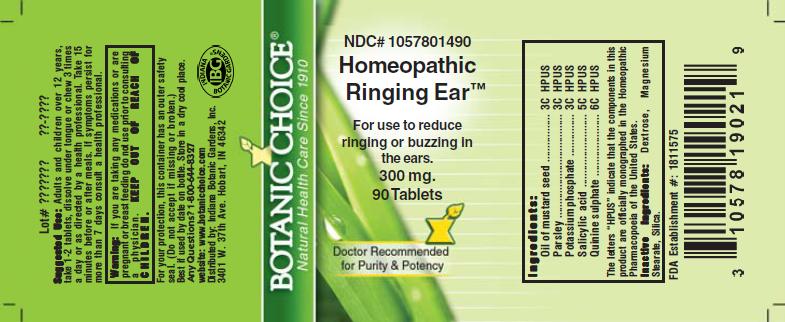 DRUG LABEL: Homeopathic Ringing Ear  Formula
NDC: 10578-014 | Form: TABLET
Manufacturer: Indiana Botanic Gardens
Category: homeopathic | Type: HUMAN OTC DRUG LABEL
Date: 20110325

ACTIVE INGREDIENTS: QUININE SULFATE 6 [hp_C]/1 1; SALICYLIC ACID 5 [hp_C]/1 1; ALLYLTHIOUREA 3 [hp_C]/1 1; PETROSELINUM CRISPUM 3 [hp_C]/1 1; POTASSIUM PHOSPHATE, DIBASIC 3 [hp_C]/1 1
INACTIVE INGREDIENTS: DEXTROSE; MAGNESIUM STEARATE ; SILICON DIOXIDE 

Homeopathic Ringing Ear Formula

ACTIVE INGREDIENT

I n g r e d i e n t s :

Oil of mustard seed...................... 3C HPUS
Parsley............................. 3C HPUS
Potassium phosphate.......................... 3C HPUS
Salicylic acid............................. 5C HPUS
Quinine sulphate...................... 6C HPUS

The letters “HPUS” indicate that the components in
this product are officially monographed in the
Homeopathic Pharmacopoeia of the United States.

PURPOSE

For use to reduce ringing or buzzing in the ears

KEEP OUT OF
REACH OF CHILDREN.

INDICATIONS AND USAGE

For use to reduce ringing or buzzing in the ears

WARNINGS

Warning: If you are taking any medications or
are pregnant or breast feeding do not use prior to
consulting a physician.

DOSAGE AND ADMINISTRATION

Suggested Use: Adults and children over 12
years, take 1-2 tablets, dissolve under tongue or
chew 3 times a day or as directed by a health care
professional. Take 15 minutes before or after meals.
If symptoms persist for more than 7 days consult a
health professional.

Inactive Ingredients: Dextrose, Magnesium
Stearate, Silica.

PACKAGE LABEL

NDC# 1057801490

Homeopathic Ringing Ear Formula

For use to reduce ringing or buzzing in the ears

300 mg.
90 Tablets

USER SAFETY WARNINGS

For your protection, this container has an outer
safety seal. (Do not accept if missing or broken.)
Best if used by date on bottle. Store in a dry cool place.
Any Questions? 1-800-644-8327
website: www.botanicchoice.com

FDA Establishment #: 1811575

Distributed by: Indiana Botanic Gardens, Inc.
3401 W. 37th Ave. Hobart, IN 46342